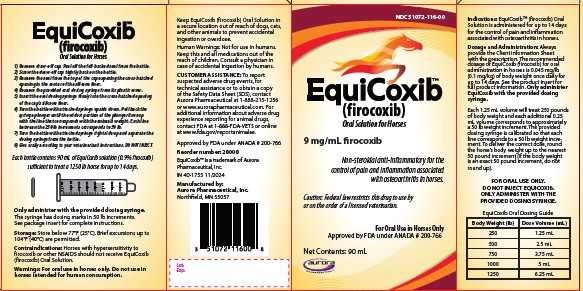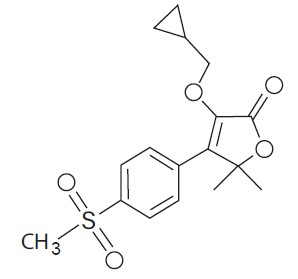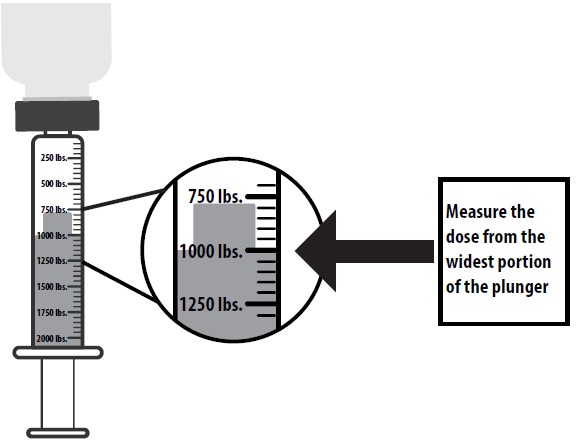 DRUG LABEL: EquiCoxib
NDC: 51072-116 | Form: SOLUTION
Manufacturer: Aurora Pharmaceutical, Inc.
Category: animal | Type: PRESCRIPTION ANIMAL DRUG LABEL
Date: 20251211

ACTIVE INGREDIENTS: firocoxib 9.0 mg/1 mL

EquiCoxib™
(firocoxib)
Oral Solution for Horses

Non-steroidal anti-inflammatory drug for oral use in horses only.

CAUTION: Federal law restricts this drug to use by or on the order of a licensed veterinarian.

Description:

EquiCoxib (firocoxib) belongs to the coxib class of non-narcotic, non-steroidal anti-inflammatory drugs (NSAIDs). Firocoxib is a white crystalline compound described chemically as 3-(cyclopropylmethoxy)-4-(4-(methylsulfonyl)phenyl)-5,5-dimethylfuranone. The empirical formula is C17H20O5S, and the molecular weight is 336.4. The structural formula is shown below:

Indications:

EquiCoxib Oral Solution is administered for up to 14 days for the control of pain and inflammation associated with osteoarthritis in horses.

Dosage and Administration:

Always provide the Client Information Sheet with the prescription. The recommended dosage of EquiCoxib (firocoxib) for oral administration in horses is 0.045 mg/lb (0.1 mg/kg) of body weight once daily for up to 14 days. In target animal safety studies, toxicity was seen at the recommended dose when the duration of treatment exceeded 30 days. Only administer EquiCoxib with the provided dosing syringe.

Each 1.25 mL volume will treat 250 pounds of body weight and each additional 0.25 mL volume corresponds to approximately a 50 lb weight increment. The provided dosing syringe is calibrated so that each line corresponds to a 50 lb weight increment. To deliver the correct dose, round the horse's body weight up to the nearest 50 pound increment (if body weight is an exact 50 pound increment, do not round up).

FOR ORAL USE ONLY. DO NOT INJECT EQUICOXIB. ONLY ADMINISTER WITH THE PROVIDED DOSING SYRINGE.

EquiCoxib Oral Dosing Guide
Body Weight (lb) | Dose Volume (mL)
250 | 1.25 mL
500 | 2.5 mL
750 | 3.75 mL
1000 | 5 mL
1250 | 6.25 mL

1) Remove draw-off cap. Peel off the foil-backed seal from the bottle.
2) Screw the draw-off cap tightly back on the bottle.
3) Remove the seal from the top of the cap exposing the cross-hatched opening in the center of the silicone liner.
4) Remove the provided oral dosing syringe from its plastic cover.
5) Insert the oral dosing syringe firmly into the cross-hatched opening of the caps silicone liner.
6) Turn the bottle with attached syringe upside down. Pull back the syringe plunger until the widest portion of the plunger lines up with the line that corresponds with the animals weight. Each line between the 250 lb increments corresponds to 50 lb.

7) Turn the bottle with attached syringe right side up and separate the dosing syringe from the bottle.
8) Give orally according to your veterinarians instructions.
DO NOT INJECT.

Contraindications:

Horses with hypersensitivity to firocoxib should not receive EquiCoxib Oral Solution.

Warnings:

For oral use in horses only. Do not use in horses intended for human consumption.

Human Warnings: Not for use in humans. Keep this and all medications out of the reach of children. Wash hands with soap and water after use. Consult a physician in case of accidental ingestion by humans.

Animal Safety: Clients should be advised to observe for signs of potential drug toxicity and be given a Client Information Sheet with each prescription.

Keep EquiCoxib in a secure location out of reach of dogs, cats, and other animals to prevent accidental ingestion or overdose.

To report suspected adverse drug events, for technical assistance or to obtain a copy of the Safety Data Sheet (SDS), contact Aurora Pharmaceutical at 1-888-215-1256 or www.aurorapharmaceutical.com. For additional information about adverse drug experience reporting for animal drugs, contact FDA at 1-888-FDA-VETS or online at www.fda.gov/reportanimalae.

Precautions:

Horses should undergo a thorough history and physical examination before initiation of NSAID therapy. Appropriate laboratory tests should be conducted to establish hematological and serum biochemical baseline data before and periodically during administration of any NSAID. Clients should be advised to observe for signs of potential drug toxicity and be given a Client Information Sheet with each prescription. See Information for Owner or Person Treating Horse section of this package insert.

Treatment with EquiCoxib should be terminated if signs such as inappetance, colic, abnormal feces, or lethargy are observed. As a class, cyclooxygenase inhibitory NSAIDs may be associated with gastrointestinal, renal, and hepatic toxicity. Sensitivity to drug-associated adverse events varies with the individual patient. Horses that have experienced adverse reactions from one NSAID may experience adverse reactions from another NSAID. Patients at greatest risk for adverse events are those that are dehydrated, on diuretic therapy, or those with existing renal, cardiovascular, and/or hepatic dysfunction. Concurrent administration of potentially nephrotoxic drugs should be carefully approached or avoided. NSAIDs may inhibit the prostaglandins that maintain normal homeostatic function. Such anti-prostaglandin effects may result in clinically significant disease in patients with underlying or pre-existing disease that has not been previously diagnosed. Since many NSAIDs possess the potential to produce gastrointestinal ulcerations and/or gastrointestinal perforation, concomitant use of EquiCoxib Oral Solution with other anti-inflammatory drugs, such as NSAIDs or corticosteroids, should be avoided. The concomitant use of protein bound drugs with EquiCoxib Oral Solution has not been studied in horses. The influence of concomitant drugs that may inhibit the metabolism of EquiCoxib Oral Solution has not been evaluated. Drug compatibility should be monitored in patients requiring adjunctive therapy. The safe use of EquiCoxib Oral Solution in horses less than one year in age, horses used for breeding, or in pregnant or lactating mares has not been evaluated. Consider appropriate washout times when switching from one NSAID to another NSAID or corticosteroid.

Adverse Reactions:

In controlled field studies, 127 horses (ages 3 to 37 years) were evaluated for safety when given firocoxib at a dose of 0.045 mg/lb (0.1 mg/kg) orally once daily for up to 14 days. The following adverse reactions were observed. Horses may have experienced more than one of the observed adverse reactions during the study.

Adverse Reactions Seen in U.S. Field Studies

Firocoxib was safely used concomitantly with other therapies, including vaccines, anthelmintics, and antibiotics, during the field studies. The safety data sheet (SDS) contains more detailed occupational safety information.

To report suspected adverse drug events, for technical assistance, or to obtain a copy of the Safety Data Sheet (SDS), contact Aurora Pharmaceutical Inc. at 1-888-215-1256 or www.aurorapharmaceutical.com. For additional
information about adverse drug experience reporting for animal drugs, contact FDA at 1-888-FDA-VETS, or online at www.fda.gov/reportanimalae.

Adverse Reactions | Firocoxib n=127 | Active Control n=125
Abdominal pain | 0 | 1
Diarrhea | 2 | 0
Excitation | 1 | 0
Lethargy | 0 | 1
Loose stool | 1 | 0
Polydipsia | 0 | 1
Urticaria | 0 | 1

Information for Owner or Person Treating Horse:

You should give a Client Information Sheet to the person treating the horse and advise them of the potential for adverse reactions and the clinical signs associated with NSAID intolerance. Adverse reactions may include erosions and ulcers of the gums, tongue, lips and face, weight loss, colic, diarrhea, or icterus. Serious adverse reactions associated with this drug class can occur without warning and, in some situations, result in death. Clients should be advised to discontinue NSAID therapy and contact their veterinarian immediately if any of these signs of intolerance are observed. The majority of patients with drug-related adverse reactions recover when the signs are recognized, drug administration is stopped, and veterinary care is initiated.

Clinical Pharmacokinetics / Pharmacodynamics:

Pharmacokinetics: When administered as a 0.045 mg/lb (0.1 mg/kg) dose in oral paste to adult horses with normal access to roughage, feed, and water, the absolute bioavailability of firocoxib from oral paste is approximately 79%. Following oral administration, drug peak concentration (Cmax) of 0.08 mcg/mL can be reached at 4 hours (Tmax) post-dosing. However, in some animals, up to 12 hours may be needed before significant plasma concentrations are observed. Little drug amount distributes into blood cells. The major metabolism mechanism of firocoxib in the horse is decyclopropylmethylation followed by glucuronidation of that metabolite. Based upon radiolabel studies, the majority of firocoxib is eliminated in the urine as the decyclopropylmethylated metabolite. Despite a high rate of plasma protein binding (98%), firocoxib exhibits a large volume of distribution (mean Vd(ss) = 1652 mL/kg). The terminal elimination half-life (T1/2) in plasma averages 30-40 hours after IV or oral paste dosing. Therefore, drug accumulation occurs with repeated dose administrations and steady state concentrations are achieved beyond
6-8 daily oral doses in the horse. Dose linearity exists from 1X-2X of 0.1 mg/kg/day.

Mode of action: EquiCoxib (firocoxib) is a cyclooxygenase-inhibiting (coxib) class, non-narcotic, non-steroidal anti-inflammatory drug (NSAID) with anti-inflammatory, analgesic and antipyretic activity^1 in animal models. Based on in vitro horse data, firocoxib is a selective inhibitor of prostaglandin biosynthesis through inhibition of inducible cyclooxygenase-2-isoenzyme (COX-2)^2. Firocoxib selectivity for the constitutive isoenzyme, cyclooxygenase-1 (COX-1) is relatively low. However, the clinical significance of these in vitro selectivity findings has not been established.

Effectiveness:

Two hundred fifty-three client-owned horses of various breeds, ranging in age from 2 to 37 years and weighing from 595 to 1638 lbs, were randomly administered firocoxib oral paste or an active control drug in multi-center field studies. Two hundred forty horses were evaluated for effectiveness and 252 horses were evaluated for safety. Horses were assessed for lameness, pain on manipulation, range of motion, joint swelling, and overall clinical improvement in a non-inferiority evaluation of firocoxib oral paste compared to an active control. At study’s end, 84.4% of horses treated with firocoxib oral paste were judged improved on veterinarians’ clinical assessment, and 73.8% were also rated improved by owners.
Horses treated with firocoxib oral paste showed improvement in veterinarian-assessed lameness, pain on manipulation, range of motion, and joint swelling that was comparable to the active control.

Animal Safety:

In a target animal safety study, firocoxib was administered orally to healthy adult horses (two male castrates and four females per group) at 0, 0.1, 0.3 and 0.5 mg firocoxib/kg body weight (1, 3 and 5X the recommended dose) for 30 days. Administration of firocoxib at 0.3 and 0.5 mg/kg body weight was associated with an increased incidence of oral ulcers as compared to the control group but, no oral ulcers were noted with 0.1 mg/kg. There were no other drug-related adverse findings in this study.

In another target animal safety study, firocoxib was administered orally to healthy adult horses (four males or male castrates and four females per group) at 0, 0.1, 0.3 and 0.5 mg firocoxib/kg body weight (1, 3 and 5X the recommended dose) for 42 days. Administration of firocoxib at 0.1, 0.3 and 0.5 mg/kg body weight was associated with delayed healing of pre-existing oral (lip, tongue, gingival) ulcers. In addition, the incidence of oral ulcers was higher in all treated groups as compared to the control group.

Clinical chemistry and coagulation abnormalities were seen in several horses in the 0.5 mg/kg (5X) group. One 5X male horse developed a mildly elevated BUN and creatinine over the course of the study, prolonged buccal mucosal bleeding time (BMBT), and a dilated pelvis of the right kidney. Another 5X male had a similar mild increase in creatinine during the study but did not have any gross abnormal findings. One female in the 5X group had a prolonged BMBT, bilateral tubulointerstitial nephropathy and bilateral papillary necrosis. Tubulointerstitial nephropathy occurred in one 3X female, two 3X male horses, and the 5X female horse discussed above with the prolonged BMBT. Papillary necrosis was present in one 1X male horse and the 5X female horse discussed above. Despite the gross and microscopic renal lesions, all of the horses were clinically healthy and had normal hematology, clinical chemistry and urinalysis values.

In another target animal safety study, firocoxib was administered orally to healthy adult horses (three females, two male castrates and one male per group) at 0, 0.25 mg/kg, 0.75 mg/kg and 1.25 mg/kg (2.5, 7.5 and 12.5X the recommended dose of 0.1 mg/kg) for 92 days. An additional group of three females, two male castrates and one male per group, was dosed at 1.25 mg/kg for 92 days but was monitored until Days 147-149. There were treatment-related adverse events in all treated groups. These consisted of ulcers of the lips, gingiva and tongue and erosions of the skin of the mandible and head. Gross and microscopic lesions of the kidneys consistent with tubulointerstitial nephropathy were seen in all treated groups. Papillary necrosis was seen in the 2.5X and 12.5X groups. In addition, several 12.5X horses had elevated liver enzymes (GGT, SDH, AST and ALT). One 2.5X horse had increased urine GGT and urine protein levels which was due to renal hemorrhage and nephropathy. Gastric ulcers of the margo plicatus and glandular area were more prevalent in the 2.5X and 7.5X groups, but not seen in the 12.5X group. The group of horses that were monitored until Days 147-149 showed partial to full recovery from oral and skin ulcers, but no recovery from tubulointerstitial nephropathy.

Storage Information:

Store below 77°F (25°C). Brief excursions up to 104°F (40°C) are permitted.

How Supplied:

EquiCoxib is available in 90 mL bottles, sufficient to treat a 1250 lb. horse for up to 14 days, and 400 mL bottles, sufficient to treat four 1250 lb. horses for up to 14 days.

References:

^1McCann ME, Rickes EL, Hora DF, Cunningham PK et al. In vitro effects and in vivo efficacy of a novel cyclooxygenase-2 inhibitor in cats with lipopolysaccharide-induced pyrexia. Am J Vet Res. 2005 Jul;66 (7):1278-84

^2McCann ME, Anderson DR, Brideau C et al. In vitro activity and in vivo efficacy of a novel COX-2 inhibitor in the horse. Proceedings of the Academy of Veterinary Internal Medicine. 2002. Abstract 114, p.789.

Marketed by: Aurora Pharmaceutical, Inc.

Northfield, MN 55057

Approved by FDA under ANADA # 200-766

EquiCoxib is a trademark of Aurora Pharmaceutical, Inc.

Client Information Sheet

EquiCoxib™

(firocoxib)

Oral Solution for Horses

Non-steroidal anti-inflammatory drug

Information for Horse Owners

EquiCoxib™ Oral Solution is administered for up to 14 days for the control of pain and inflammation associated with osteoarthritis in horses.

This summary contains important information about EquiCoxib. You should read this information before you start giving your horse EquiCoxib Oral Solution and review it each time your prescription is refilled. This sheet is provided only as a summary and does not take the place of instructions from your veterinarian. Talk to your veterinarian if you do not understand any of this information or you want to know more about EquiCoxib.

What is EquiCoxib?

EquiCoxib is a veterinary prescription non-steroidal anti-inflammatory drug (NSAID) of the coxib class used to control pain and inflammation associated with osteoarthritis in horses. Osteoarthritis (OA) is a painful condition caused by progressive "wear and tear" of cartilage and other parts of the joints that may result in the following changes or signs in your horse:

- Limping or lameness.
- Decreased activity or exercise (reluctance to stand, walk, trot or run, or difficulty in performing these activities).
- Stiffness or decreased movement of joints.

How to give EquiCoxib to your horse.

EquiCoxib should be given according to your veterinarian's instructions. Do not change the way you give EquiCoxib to your horse without first speaking with your veterinarian.
Do not exceed 14 days of treatment.
The recommended dosage of EquiCoxib (firocoxib) for oral administration in horses is 0.045 mg/lb (0.1 mg/kg) of body weight once daily for up to 14 days.
Each 1.25 mL volume will treat 250 pounds of body weight and each additional 0.25 mL corresponds to 50 lb weight increment. To deliver the correct dose, round the horse's body weight up to the nearest 50 pound increment (if the body weight is an exact 50 pound increment, do not round up). EquiCoxib may be given with or without food.

What kind of results can I expect when my horse is on EquiCoxib for OA?

While EquiCoxib is not a cure for osteoarthritis, it can control the pain and inflammation associated with OA and can improve your horse's mobility.

- Response varies from horse to horse, but improvement can be quite dramatic.
- Improvement can be seen in just a few hours in most horses.

Which horses should not receive EquiCoxib?

Your horse should not be given EquiCoxib if he/she:

- Has an allergic reaction to firocoxib, the active ingredient in EquiCoxib.
- Has previously had an allergic reaction (such as hives, facial or lower limb swelling, or red or itchy skin) to aspirin or other NSAIDs.
- Is presently taking aspirin, phenylbutazone, flunixin meglumine, diclofenac, ketoprofen, or other NSAIDs or corticosteroids.
- The safety of EquiCoxib has not been determined in horses less than one year of age or in breeding horses, pregnant or lactating mares.

EquiCoxib Oral Solution should only be given orally to horses.

- EquiCoxib is not for use in horses intended for human food consumption.
- People should not take EquiCoxib. Keep EquiCoxib and all medications out of the reach of children. Consult a physician in case of accidental ingestion by humans.

What to tell/ask your veterinarian before giving EquiCoxib.

Talk to your veterinarian about:

- The signs of OA you have observed in your horse, such as limping or stiffness.
- If any tests, such as X-rays, will be done before EquiCoxib is prescribed.
- How often your horse may need to be examined by your veterinarian.
- The risks and benefits of using EquiCoxib.

Tell your veterinarian if your horse has ever had the following medical problems:

- Any side effects from taking EquiCoxib or other NSAIDs, such as aspirin or phenylbutazone.
- Any kidney disease.
- Any liver disease.
- Any gastrointestinal ulcers.

Tell your veterinarian about:

- Other medical problems or allergies that your horse has now, or has had in the past.
- All medicines that you are giving or plan to give to your horse, including those you can get without a prescription and any dietary supplements.

Tell your veterinarian if you plan to breed your horse, or if your mare is pregnant or nursing a foal.

What are the possible side effects that may occur in my horse during EquiCoxib therapy?

EquiCoxib, like other NSAIDS, may cause some side effects. Serious side effects associated with NSAID therapy in horses can occur with or without warning. The most common side effects associated with EquiCoxib therapy involve the tongue, lips and skin of the mouth and face (erosions and ulcers of the mucosa and skin) and the kidney. Gastrointestinal, kidney and liver problems have also been reported with other NSAIDs. Look for the following side effects that may indicate your horse is having a problem with EquiCoxib or may have another medical problem:

- Sores or ulcers on the tongue and inside of mouth.
- Sores, scabs, redness, or rubbing of the facial skin, particularly around the mouth.
- Change in eating or drinking habits (frequency or amount consumed).
- Change in urination habits (frequency or color).
- Yellowing of gums, skin, or whites of the eyes (jaundice).
- Unexpected weight loss.
- Change in behavior (such as increased or decreased activity level).

It is important to stop therapy and contact your veterinarian if you think your horse has a medical problem or side effect while taking EquiCoxib Oral Solution. If you have additional questions about possible side effects, talk with your veterinarian or call 1-888-215-1256.

Can EquiCoxib be given with other medications?

EquiCoxib should not be given with other NSAIDs (for example, aspirin, phenylbutazone, diclofenac, ketoprofen or flunixin) or systemic corticosteroids (for example, prednisone, cortisone, dexamethasone, or triamcinolone). Tell your veterinarian about all medications that you have given your horse in the past, and any medications you are planning to give with EquiCoxib Oral Solution. This should include other medicines that you can get without a prescription or any dietary supplements. Your veterinarian may want to check that all of your horse's medicines can be given together.

What do I do in case my horse receives more than the prescribed amount of EquiCoxib?

- Consult your veterinarian if your horse receives more than the prescribed amount of EquiCoxib.

What else should I know about EquiCoxib?

- This sheet provides a summary of information about EquiCoxib Oral Solution and general information about NSAIDs. If you have any questions or concerns about EquiCoxib or osteoarthritis pain, talk with your veterinarian.
- As with all prescribed medicines, EquiCoxib Oral Solution should only be given to the horse for which it is prescribed. It should be given to your horse only for the condition for which it is prescribed, at the labeled dose and duration.
- It is important to periodically discuss your horse's response to EquiCoxib Oral Solution. Your veterinarian will determine if your horse is responding as expected and if your horse should continue receiving EquiCoxib Oral Solution.

DOSAGE AND ADMINISTRATION:

Always provide the Client Information Sheet with the prescription. The recommended dosage of EquiCoxib (firocoxib) for oral administration in horses is 0.045 mg/lb (0.1 mg/kg) of body weight once daily for up to 14 days. In target animal safety studies, toxicity was seen at the recommended dose when the duration of treatment exceeded 30 days. Only administer EquiCoxib with the provided dosing syringe.

Each 1.25 mL volume will treat 250 pounds of body weight and each additional 0.25 mL volume corresponds to approximately a 50 lb weight increment. The provided dosing syringe is calibrated so that each line corresponds to a 50 lb weight increment. To deliver the correct dose, round the horse's body weight up to the nearest 50 pound increment (if body weight is an exact 50 pound increment, do not round up).

FOR ORAL USE ONLY. DO NOT INJECT EQUICOXIB.

ONLY ADMINISTER WITH THE PROVIDED

DOSING SYRINGE.

EquiCoxib Oral Dosing Guide
Body Weight (lb) | Dose Volume (mL)
250 | 1.25 mL
500 | 2.5 mL
750 | 3.75 mL
1000 | 5 mL
1250 | 6.25 mL

1) Remove draw-off cap. Peel off the foil-backed seal from the bottle.

2) Screw the draw-off cap tightly back on the bottle.
3) Remove the seal from the top of the cap exposing the cross-hatched opening in the center of the silicone liner.
4) Remove the provided oral dosing syringe from its plastic cover.
5) Insert the oral dosing syringe firmly into the cross-hatched
opening of the caps silicone liner.
6) Turn the bottle with attached syringe upside down. Pull back the syringe plunger until the widest portion of the plunger lines up with the line that corresponds with the animals weight. Each line between the 250 lb increments corresponds to 50 lb.

7) Turn the bottle with attached syringe right side up and separate the dosing syringe from the bottle.

8) Give orally according to your veterinarians instructions.
DO NOT INJECT.

Principal Display Panel – 90mL Bottle Carton

Approved by FDA under ANADA # 200-766

EquiCoxib™
(firocoxib)

Non-steroidal anti-inflammatory for the control of pain and inflammation associated with osteoarthritis in horses.

Caution: Federal law restricts this drug to use by or on the order of a licensed veterinarian.

Net Contents: 90 mL
Oral Solution for Horses

IN 40-1755 11/2024